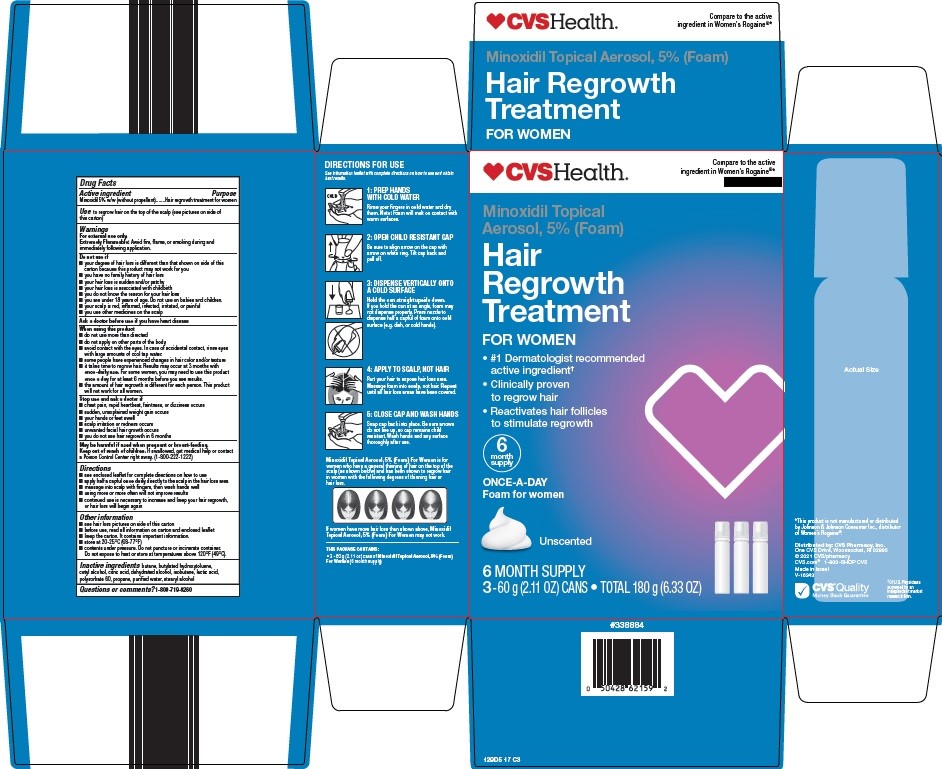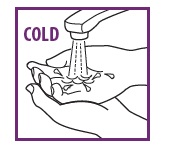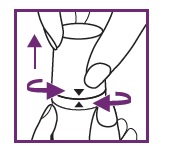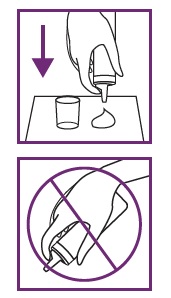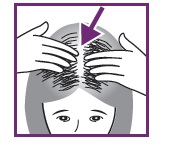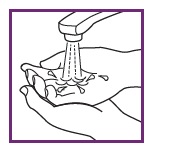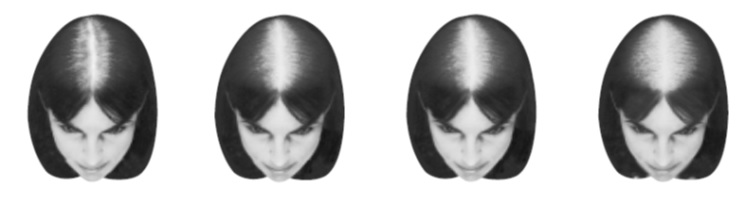 DRUG LABEL: hair regrowth treatment
NDC: 59368-315 | Form: AEROSOL, FOAM
Manufacturer: Sixarp, LLC
Category: otc | Type: HUMAN OTC DRUG LABEL
Date: 20250919

ACTIVE INGREDIENTS: MINOXIDIL 50 mg/1 g
INACTIVE INGREDIENTS: BUTYLATED HYDROXYTOLUENE; CETYL ALCOHOL; CITRIC ACID MONOHYDRATE; ALCOHOL; ISOBUTANE; LACTIC ACID, UNSPECIFIED FORM; POLYSORBATE 60; WATER; STEARYL ALCOHOL

CVS Pharmacy, Inc. Hair Regrowth Treatment Drug Facts

Active ingredient

Minoxidil 5% w/w (without propellant)

Purpose

Hair regrowth treatment for women

Use

to regrow hair on the top of the scalp (see pictures on side of this carton)

Warnings

For external use only.

Extremely Flammable:Avoid fire, flame, or smoking during and immediately following application.

Do not use if

- your degree of hair loss is different than that shown on side of this carton because this product may not work for you
- you have no family history of hair loss
- your hair loss is sudden and/or patchy
- your hair loss is associated with childbirth
- you do not know the reason for your hair loss
- you are under 18 years of age. Do not use on babies and children.
- your scalp is red, inflamed, infected, irritated, or painful
- you use other medicines on the scalp

Ask a doctor before use if you have

heart disease

When using this product

- do not use more than directed
- do not apply on other parts of the body
- avoid contact with the eyes. In case of accidental contact, rinse eyes with large amounts of cool tap water.
- some people have experienced changes in hair color and/or texture
- it takes time to regrow hair. Results may occur at 3 months with once-daily use. For some women, you may need to use this product once a dayfor at least 6 months before you see results.
- the amount of hair regrowth is different for each person. This product will not work for all women.

Stop use and ask a doctor if

- chest pain, rapid heartbeat, faintness, or dizziness occurs
- sudden, unexplained weight gain occurs
- your hands or feet swell
- scalp irritation or redness occurs
- unwanted facial hair growth occurs
- you do not see hair regrowth in 6 months

Keep out of reach of children.

If swallowed, get medical help or contact a Poison Control Center right away. (1-800-222-1222)

Directions

- see enclosed leaflet for complete directions on how to use
- apply half a capful once dailydirectly to the scalp in the hair loss area
- massage into scalp with fingers, then wash hands well
- using more or more often will not improve results
- continued use is necessary to increase and keep your hair regrowth, or hair loss will begin again

Other information

- see hair loss pictures on side of this carton
- before use, read all information on carton and enclosed leaflet
- keep the carton. It contains important information.
- store at 20-25°C (68-77°F)
- contents under pressure. Do not puncture or incinerate container. Do not expose to heat or store at temperatures above 120°F (49°C).

Inactive ingredients

butane, butylated hydroxytoluene, cetyl alcohol, citric acid, dehydrated alcohol, isobutane, lactic acid, polysorbate 60, propane, purified water, stearyl alcohol

Questions or comments?

1-800-719-9260

Consumer Information

#1 DERMATOLOGIST RECOMMENDED ACTIVE INGREDIENT†

IMPORTANT INFORMATION ABOUT

Minoxidil Topical Aerosol, 5% (Foam)

Hair Regrowth Treatment

For Women

- Reactivates Hair Follicles To Stimulate Regrowth
- Clinically Proven to Regrow Hair
- Once-a-Day Foam For Women

UNSCENTED

SAVE THIS LEAFLET FOR FUTURE REFERENCE

Please read this leaflet carefully. It will help you understand how to use Minoxidil Topical Aerosol, 5% (For Women) and what to expect from its use. It takes time to regrow hair. Results may occur at 3 months with once dailyusage. For some women, you may need to use this product for at least 6 months before you see results. If you have any questions after reading this leaflet, or anytime while using Minoxidil Topical Aerosol, 5% (For Women), you should ask your health care professional or call us at 1-800-719-9260.

WHAT IS MINOXIDIL TOPICAL AEROSOL, 5% (FOR WOMEN)?

Minoxidil Topical Aerosol, 5% (For Women) is a white foam containing 5% minoxidil for use only on the scalp to help regrow hair in women.

WHO MAY USE MINOXIDIL TOPICAL AEROSOL, 5% (FOR WOMEN)?

Minoxidil Topical Aerosol, 5% (For Women) may be appropriate for you if you are an adult who is at least 18 years old and experiencing gradually thinning hair or gradual hair loss on the top of your scalp. The common hereditary thinning or hair loss process begins slowly and may become noticeable only after years of gradual loss.

Minoxidil Topical Aerosol, 5% (For Women) is for general thinning of hair on the top of the scalp as shown. Minoxidil Topical Aerosol, 5% (For Women) has been shown to regrow hair in women with the degrees of hair loss shown. If women have more hair loss than shown, Minoxidil Topical Aerosol, 5% (For Women) may not work.

Many of those experiencing hair loss have other family members with gradual thinning of hair or hair loss. If there is no family history of gradual thinning or gradual hair loss, or hair loss is patchy, see your doctor.

WHO SHOULD NOT USE MINOXIDIL TOPICAL AEROSOL, 5% (FOR WOMEN)?

Minoxidil Topical Aerosol, 5% (For Women) will not prevent or improve hair loss related to pregnancy, the use of some prescription and non-prescription medications, certain severe nutritional problems (very low body iron; excessive vitamin A intake), the recently discontinued use of birth control pills, low thyroid states (hypothyroidism), chemotherapy, or diseases which cause scarring of the scalp. Also, Minoxidil Topical Aerosol, 5% (For Women) will not improve hair loss due to:

- Damage from the use of hair care products which cause scarring or deep burns of the scalp.
- Hair grooming methods such as cornrowing or ponytails which require pulling the hair tightly back from the scalp.

Do not use if you are not sure of the reason for your hair loss.

WILL MINOXIDIL TOPICAL AEROSOL, 5% (FOR WOMEN) WORK FOR ME?

The amount of hair regrowth is different for each person. Not everyone will respond to Minoxidil Topical Aerosol, 5% (For Women). The response to Minoxidil Topical Aerosol, 5% (For Women) cannot be predicted. No one will be able to grow back all their hair.

To see your best results with Minoxidil Topical Aerosol, 5% (For Women), make sure you apply the product directly to the scalp once daily. For some women, Minoxidil Topical Aerosol, 5% (For Women) may not work.

HOW SOON CAN I EXPECT RESULTS FROM USING MINOXIDIL TOPICAL AEROSOL, 5% (FOR WOMEN)?

Since normal hair usually grows only 1/2 to 1 inch per month, hair regrowth with Minoxidil Topical Aerosol, 5% (For Women) also takes time. Generally, new hair growth is slow for a Minoxidil Topical Aerosol, 5% (For Women) user. Results may be seen as early as 3 months with once dailyuse. For some women, it may take at least 6 months for results to be seen. If you do not see any results after 6 months, stop using Minoxidil Topical Aerosol, 5% (For Women) and seek the advice of your doctor.

When you first begin to use Minoxidil Topical Aerosol, 5% (For Women), your hair loss may continue for up to 2 weeks. This increase in hair loss is expected and is temporary. However, if it continues after two weeks, see your physician.

IF MINOXIDIL TOPICAL AEROSOL, 5% (FOR WOMEN) IS WORKING, WHAT WILL THE HAIR LOOK LIKE?

At first, hair growth may be soft, downy, and colorless hairs. After further use, the new hairs should be the same color and thickness as the other hairs on your scalp.

HOW LONG DO I NEED TO USE MINOXIDIL TOPICAL AEROSOL, 5% (FOR WOMEN)?

If you respond to Minoxidil Topical Aerosol, 5% (For Women), you need to use it once dailyto keep and continue the hair regrowth. Up to 3 months of usage may be needed to see your best results from Minoxidil Topical Aerosol, 5% (For Women).

WHAT HAPPENS IF I COMPLETELY STOP USING MINOXIDIL TOPICAL AEROSOL, 5% (FOR WOMEN)? WILL I KEEP THE NEW HAIR?

Continuous use of Minoxidil Topical Aerosol, 5% (For Women) is needed to maintain hair regrowth. If you stop using Minoxidil Topical Aerosol, 5% (For Women), the normal hair loss process will start again. You will probably lose your newly regrown hair in three to four months.

HOW DO I USE MINOXIDIL TOPICAL AEROSOL, 5% (FOR WOMEN)?

For best results, apply half a capful once a daydirectly to the scalp in the hair loss area. Using more than the recommended amount will not improve results. Each can should last two months, if used as directed. Never take this product by mouth or apply to other parts of the body. Please refer to the “Directions for Use” section of this leaflet.

WHEN DO I USE MINOXIDIL TOPICAL AEROSOL, 5% (FOR WOMEN)?

Apply Minoxidil Topical Aerosol, 5% (For Women) once daily. If you apply at night, allow application to dry completely before going to bed.

WHAT IF I FORGET TO USE MINOXIDIL TOPICAL AEROSOL, 5% (FOR WOMEN) OR MISS A DOSE?

If you miss one daily dose of Minoxidil Topical Aerosol, 5% (For Women), just continue with your next dose. You should not make up for missed doses.

CAN I USE MINOXIDIL TOPICAL AEROSOL, 5% (FOR WOMEN) MORE THAN ONCE A DAY? WILL IT WORK FASTER, BETTER?

No. Minoxidil Topical Aerosol, 5% (For Women) will not work faster or better if used more than once a day. More frequent use or larger doses have not been shown to speed up hair growth and may increase your chances of side effects.

WHAT KIND OF SHAMPOO SHOULD I USE WITH MINOXIDIL TOPICAL AEROSOL, 5% (FOR WOMEN)?

If you wash your scalp before applying Minoxidil Topical Aerosol, 5% (For Women), use a mild shampoo.

CAN I USE HAIR SPRAYS, MOUSSES, CONDITIONERS, GELS, ETC.?

Yes. There is no reason to change your usual hair care routine when using Minoxidil Topical Aerosol, 5% (For Women). However, you should apply Minoxidil Topical Aerosol, 5% (For Women) first and wait for it to dry before applying your styling aids.

CAN I HAVE MY HAIR COLORED OR PERMED OR USE HAIR RELAXERS WHILE USING MINOXIDIL TOPICAL AEROSOL, 5% (FOR WOMEN)?

Yes. We have no evidence that coloring, perming, or using relaxers on your hair change the effect of Minoxidil Topical Aerosol, 5% (For Women). However, because the use of a permanent wave and hair color can cause scalp irritation on certain people, we recommend the following precautions:

1. To avoid possible scalp irritation, you should make sure all of the Minoxidil Topical Aerosol, 5% (For Women) has been washed off the hair and scalp before using color or perm chemicals.
2. For best results, do not apply Minoxidil Topical Aerosol, 5% (For Women) on the same day that you use a chemical treatment on your hair.
3. Do not use Minoxidil Topical Aerosol, 5% (For Women) for 24 hours after using any chemicals to make sure your scalp has not been irritated by the perm or color treatment. If no irritation occurs, continue use of Minoxidil Topical Aerosol, 5% (For Women) as usual.
4. Simply restart your normal Minoxidil Topical Aerosol, 5% (For Women) routine. There is no need to use more Minoxidil Topical Aerosol, 5% (For Women) to make up for missed applications.

Missing one day of Minoxidil Topical Aerosol, 5% (For Women) will not affect your hair regrowth results.

CAN I APPLY MINOXIDIL TOPICAL AEROSOL, 5% (FOR WOMEN) AND WASH MY HAIR AN HOUR LATER?

No. For Minoxidil Topical Aerosol, 5% (For Women) to work best, you should allow Minoxidil Topical Aerosol, 5% (For Women) to remain on the scalp for about 4 hours before washing.

DIRECTIONS FOR USE

- Please familiarize yourself with the instructions below in order to help make your product application a success.
- This product should be used ONCE DAILY, EVERY DAY.
- To be effective, it is important to apply the product DIRECTLY TO YOUR SCALP and NOT TO YOUR HAIR so that it can easily get to your hair follicles to help regrow your hair.
- There is no need to shampoo your hair before using the product. If you wish to shampoo your hair before applying Minoxidil Topical Aerosol, 5% (For Women), towel dry your hair so that the skin on the scalp is dry.

1: PREP HANDS WITH COLD WATER

Rinse your fingers in cold water and dry them. Note:Foam will melt on contact with warm surfaces.

2: OPEN CHILD RESISTANT CAP

Be sure to align arrow on the cap with arrow on white ring. Tilt cap back and pull off.

3: DISPENSE VERTICALLY ONTO A COLD SURFACE

Hold the can straight upside down.If you hold the can at an angle, foam may not dispense properly. Press nozzle to dispense half a capful of foam onto coldsurface (e.g. dish, or cold hands).

4: APPLY TO SCALP, NOT HAIR

Part your hair to expose hair loss area. Massage foam into scalp, not hair. Repeatuntil all hair loss areas have been covered.

5: CLOSE CAP AND WASH HANDS

Snap cap back into place. Be sure arrows do not line up, so cap remains child resistant. Wash hands and any surface thoroughly after use.

ARE THERE ANY SPECIAL WARNINGS ABOUT THE USE OF MINOXIDIL TOPICAL AEROSOL, 5% (FOR WOMEN)?

Warnings:

For external use only.

Extremely Flammable:Avoid fire, flame, or smoking during or immediately following application.

DO NOT USE IF

- your degree of hair loss is more than that shown on the other side of this leaflet, because this product may not work for you
- you have no family history of hair loss
- your hair loss is sudden and/or patchy
- your hair loss is associated with childbirth
- you do not know the reason for your hair loss
- you are under 18 years of age. Do not use on babies and children.
- your scalp is red, inflamed, infected, irritated, or painful
- you use other medicines on the scalp

Ask a doctor before use if you have heart disease.

WHEN USING THIS PRODUCT

- do not use more than directed
- do not apply on other parts of the body
- avoid contact with the eyes. In case of accidental contact, rinse eyes with large amounts of cool tap water.
- some people have experienced changes in hair color and/or texture
- it takes time to regrow hair. Results may occur in 3 months with once dailyuse. For some women you may need to use this product once dailyfor at least 6 months before you see results.
- the amount of hair regrowth is different for each person. This product will not work for everyone.

STOP USE AND ASK A DOCTOR IF

- chest pain, rapid heartbeat, faintness, or dizziness occurs
- sudden, unexplained weight gain occurs
- your hands or feet swell
- scalp irritation or redness occurs
- unwanted facial hair growth occurs
- you do not see hair regrowth in 6 months

May be harmful if used when pregnant or breast-feeding.

Keep out of reach of children.If swallowed, get medical help or contact a Poison Control Center right away. (1-800-222-1222)

WHAT ARE THE MOST COMMON SIDE EFFECTS WITH MINOXIDIL TOPICAL AEROSOL, 5% (FOR WOMEN)?

The most common side effects are itching and other skin irritations of the treated area of the scalp. Minoxidil Topical Aerosol, 5% (For Women) contains alcohol, which would cause burning or irritation of the eyes or sensitive skin areas. If Minoxidil Topical Aerosol, 5% (For Women) accidentally gets into these areas, rinse with large amounts of cool tap water. Stop using Minoxidil Topical Aerosol, 5% (For Women) and contact your doctor if irritation persists.

CAN MINOXIDIL TOPICAL AEROSOL, 5% (FOR WOMEN) PRODUCE UNWANTED HAIR?

Unwanted hair growth has been reported on the face and on other parts of the body with Minoxidil Topical Aerosol, 5% (For Women) use. The unwanted hair growth may be caused by the transfer of Minoxidil Topical Aerosol, 5% (For Women) to areas other than the scalp, or by absorption into the circulatory system of low levels of the active ingredient, or by a medical condition not related to the use of Minoxidil Topical Aerosol, 5% (For Women).

If you experience unwanted hair, discontinue using Minoxidil Topical Aerosol, 5% (For Women) and see your doctor for recommendations about appropriate treatment. After stopping use of Minoxidil Topical Aerosol, 5% (For Women), the unwanted hair, if caused by the use of Minoxidil Topical Aerosol, 5% (For Women), should go away over time. You can take steps to decrease the chances for unwanted hair growth:

1. Limit the application of Minoxidil Topical Aerosol, 5% (For Women) only to the scalp,
2. If you use the hands to apply Minoxidil Topical Aerosol, 5% (For Women), wash your hands thoroughly afterwards, and
3. Allow sufficient drying time before going to bed (usually 2 to 4 hours before going to bed after applying Minoxidil Topical Aerosol, 5% (For Women)).

CAN I USE MINOXIDIL TOPICAL AEROSOL, 5% (FOR WOMEN) FOR BALDNESS OR HAIR LOSS IN BABIES AND CHILDREN?

No. Minoxidil Topical Aerosol, 5% (For Women) must not be used to treat baldness or hair loss in babies or children.

WHAT FACTORS MAY INCREASE THE RISK OF SERIOUS SIDE EFFECTS WITH MINOXIDIL TOPICAL AEROSOL, 5% (FOR WOMEN)?

Minoxidil Topical Aerosol, 5% (For Women) should be applied only to the scalp. The risk of side effects may be greater when Minoxidil Topical Aerosol, 5% (For Women) is applied to other parts of the body.

If you have any other questions, ask your health care professional or call us at 1-800-719-9260.

Store at 20° to 25°C (68° to 77°F).

Contents under pressure. Do not puncture or incinerate container. Do not expose to heat or store at temperatures above 120°F (49°C).

Save this leaflet for future reference.

†Of U.S. Physicians surveyed by an independent market research firm.

Made in Israel

Distributed By

Perrigo®

Allegan, MI 49010

Rev 08-21

: 12900 00 J4

Package/Label Principal Display Panel

CVS Health®

Compare to the active ingredient in Women’s Rogaine®

Minoxidil Topical Aerosol, 5% (Foam)

Hair Regrowth Treatment

FOR WOMEN

• #1 Dermatologist recommended active ingredient

• Clinically proven to regrow hair

• Reactivates hair follicles to stimulate regrowth

6 month supply

ONCE-A-DAY

Foam for women

Unscented

6 MONTH SUPPLY

3-60 g (2.11 OZ) CANS • TOTAL 180 g (6.33 OZ)